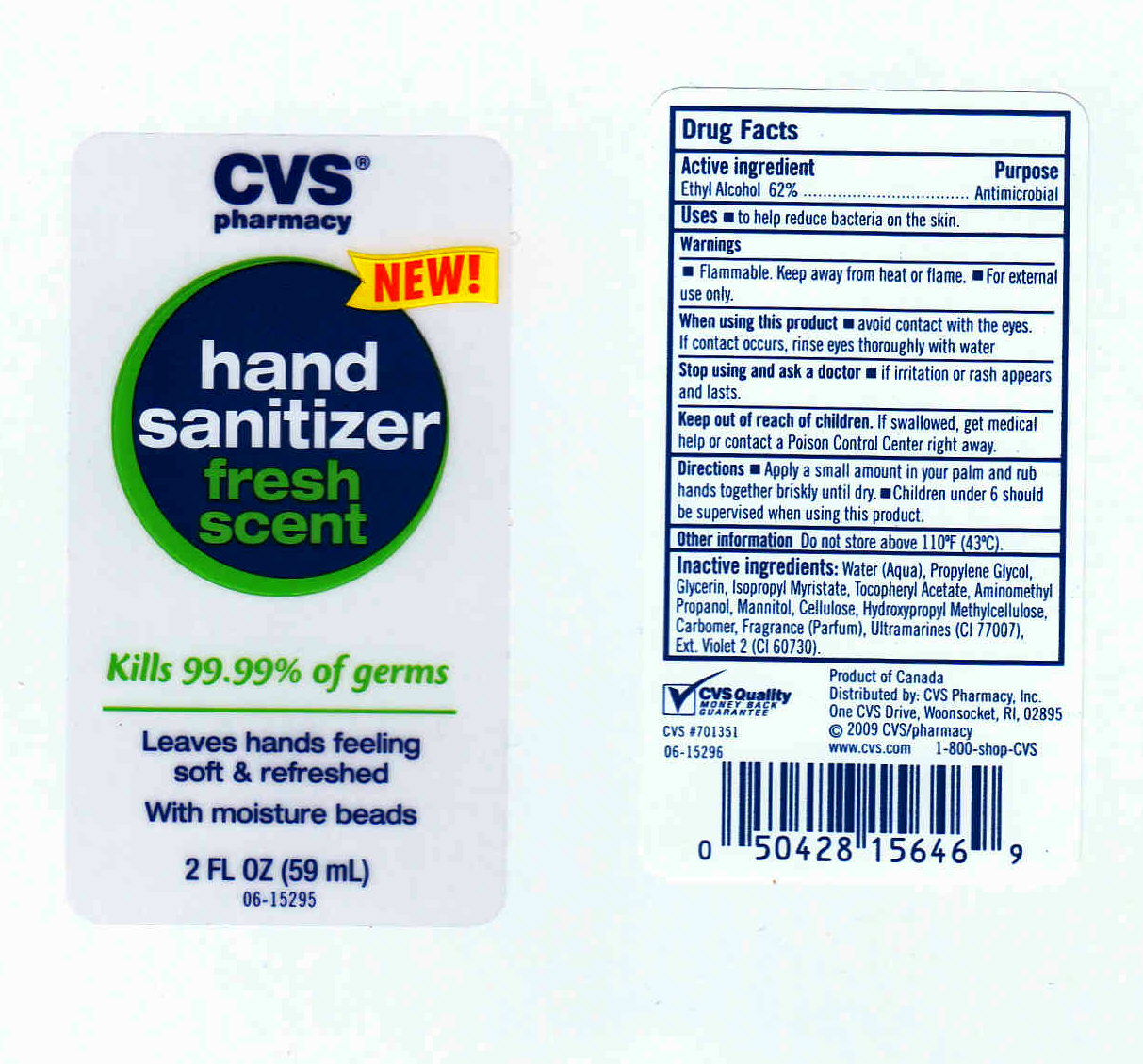 DRUG LABEL: CVS PHARMACY 
NDC: 63148-250 | Form: GEL
Manufacturer: Apollo Health and Beauty Care
Category: otc | Type: HUMAN OTC DRUG LABEL
Date: 20091010

ACTIVE INGREDIENTS: ALCOHOL 62.00 mL/100 mL
INACTIVE INGREDIENTS: WATER 36.11 mL/100 mL; PROPYLENE GLYCOL 1.00 mL/100 mL; GLYCERIN 0.20 mL/100 mL; CARBOMER HOMOPOLYMER TYPE C 0.30 mL/100 mL; 2-AMINO-2-METHYL-1-PROPANOL 0.12 mL/100 mL; ISOPROPYL MYRISTATE 0.01 mL/100 mL; MANNITOL 0.01 mL/100 mL; ALPHA-TOCOPHEROL ACETATE 0.01 mL/100 mL; POWDERED CELLULOSE 0.10 mL/100 mL; HYPROMELLOSE 0.10 mL/100 mL; EXT. D&C VIOLET NO. 2 0.04 mL/100 mL

CVS PHARMACY HAND SANITIZER FRESH SCENT

ACTIVE INGREDIENT

ETHYL ALCOHOL 62% (ANTISEPTIC)

USES

TO HELP REDUCE BACTERIA ON THE SKIN

WARNINGS

- FOR EXTERNAL USE ONLY.
- FLAMMABLE. KEEP AWAY FROM FIRE OR FLAME.

WHEN USING THIS PRODUCT

AVOID CONTACT WITH EYES. IF CONTACT OCCURS, RINSE WITH WATER.

STOP USE AND ASK A DOCTOR IF

SKIN IRRITATION OR REDNESS DEVELOPS.

KEEP OUT OF REACH OF CHILDREN

IN CASE OF ACCIDENTAL INGESTION, GET MEDICAL HELP OR CONTACT A POISON CONTROL CENTER IMMEDIATELY.

OTHER INFORMATION

STORE AT A TEMPERATURE BELOW 110^0F (43^0C).

PACKAGE FRONT AND BACK LABELS

- MM1: 2OZ LABELS, Labels2.jpg